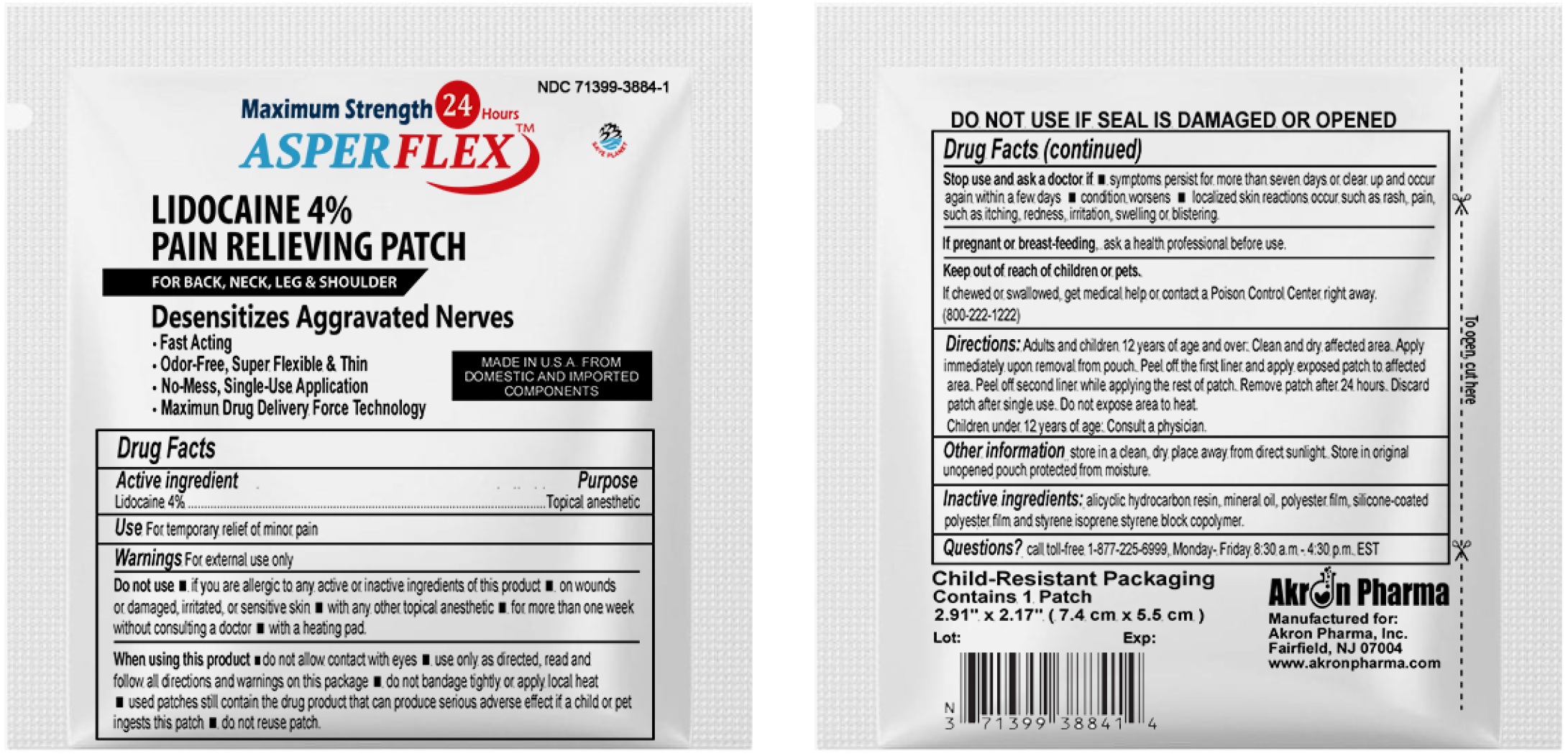 DRUG LABEL: ASPERFLEX 24HRS
NDC: 71399-3884 | Form: PATCH
Manufacturer: Akron Pharma Inc.
Category: otc | Type: HUMAN OTC DRUG LABEL
Date: 20230212

ACTIVE INGREDIENTS: LIDOCAINE 40 mg/1 1
INACTIVE INGREDIENTS: MINERAL OIL; STYRENE/ISOPRENE/STYRENE BLOCK COPOLYMER

ASPERFLEX 24 Hour Lidocaine Patch

Active Ingredient

Lidocaine 4% . . . . . . . . . . . . . . . . . . . . . . . . . . . . . . Topical Anesthetic

Purpose

Temporarily relieves minor pain.

Dosage and Administration

Directions Adults and children over 12 years:

- clean and dry affected area
- carefully remove backing from patch starting at corner
- apply sticky side of patch to affected area
- use one patch for up to 24 hours. Discard patch after single use. Children under 12 years of age: consult a physician.

Warnings

For external use only.

Idications and Usage

Uses: Temporaily relieves minor pains.

When using this product

- use only as directed
- read and follow all directions and warnings on this carton
- do not allow contact with the eyes
- do not use at the same time as other topical analgesics
- do not bandage tightly or apply local heat (such as heating pads) to the area of use
- do not microwave
- dispose of used patch in manner that always keeps product away from children and pets. Used patches still contain the drug product that can produce serious adverse effects if a child or pet chews or ingests this patch.

Stop use and consult a doctor

- condition worsens
- redness is present
- irritation develops
- symptoms persist for more than 7 days or clear up and occur again within a few days
- you experience signs of skin injury, such as pain, swelling or blistering where the product was applied.

If pregnant or breastfeeding, ask a health professional before use.

Do not Use

- condition worsens
- redness is present
- irritation develops
- symptoms persist for more than 7 days or clear up and occur again within a few days
- you experience signs of skin injury, such as pain, swelling or blistering where the product was applied.

Keep out of reach of children and pets.

If swallowed, get medical help or contact a Poison Control Center right away 800-222-1222

Other Safety Information

Store in a clean, dry place outside of direct sunlight. Protect from excessive moisture.

Inactive Ingredients

Alicyclic Hydrocarbon Resin, Mineral Oil, Polyester film, Silicone –coated polyester film and styrene isoprene styrene block copolymer

NDC: 71399-3884-6

Package size: 6 Patches

Questions?

Please Call 1(877) 225-6999

Manufactured for:
Akron Pharma, Inc.
Fairfield, NJ 07004
Manufactured in U.S.A